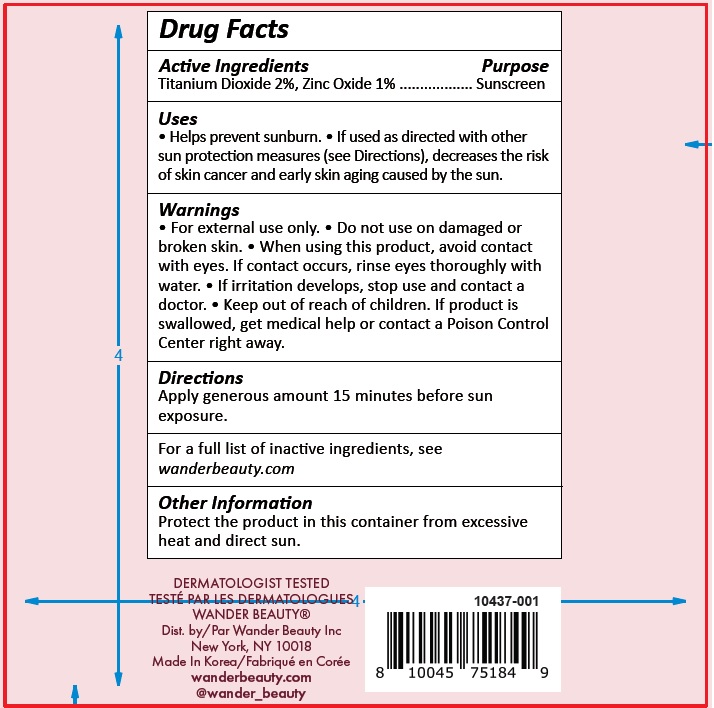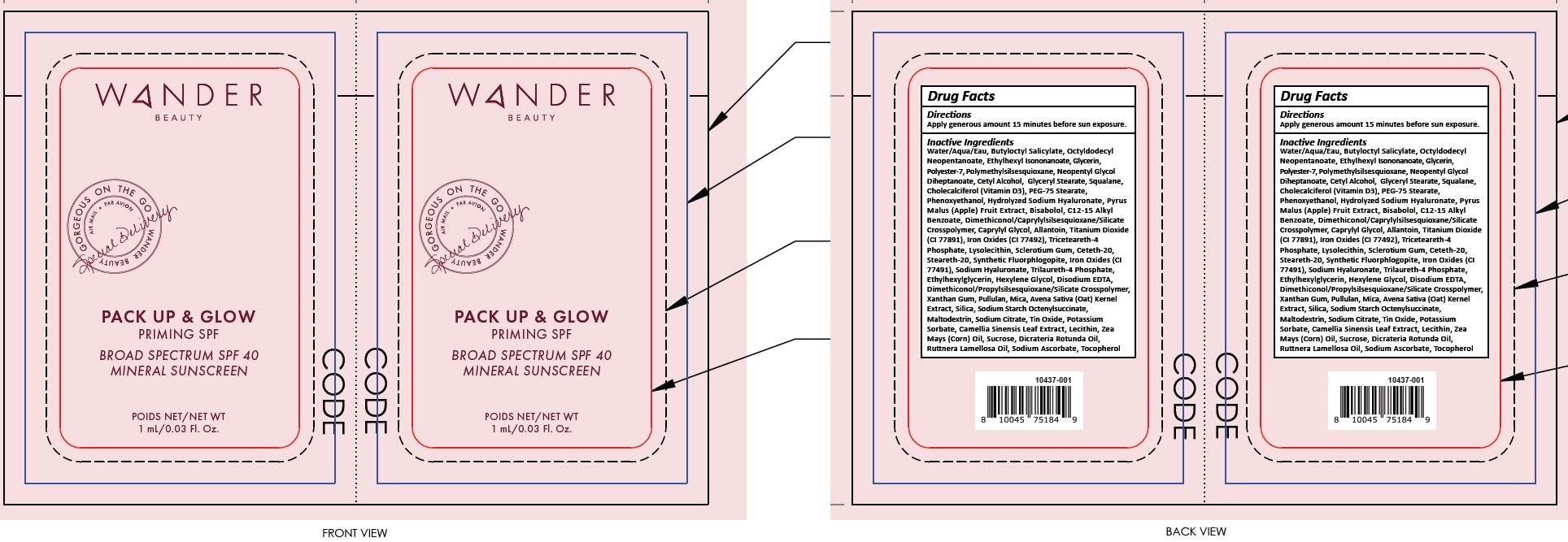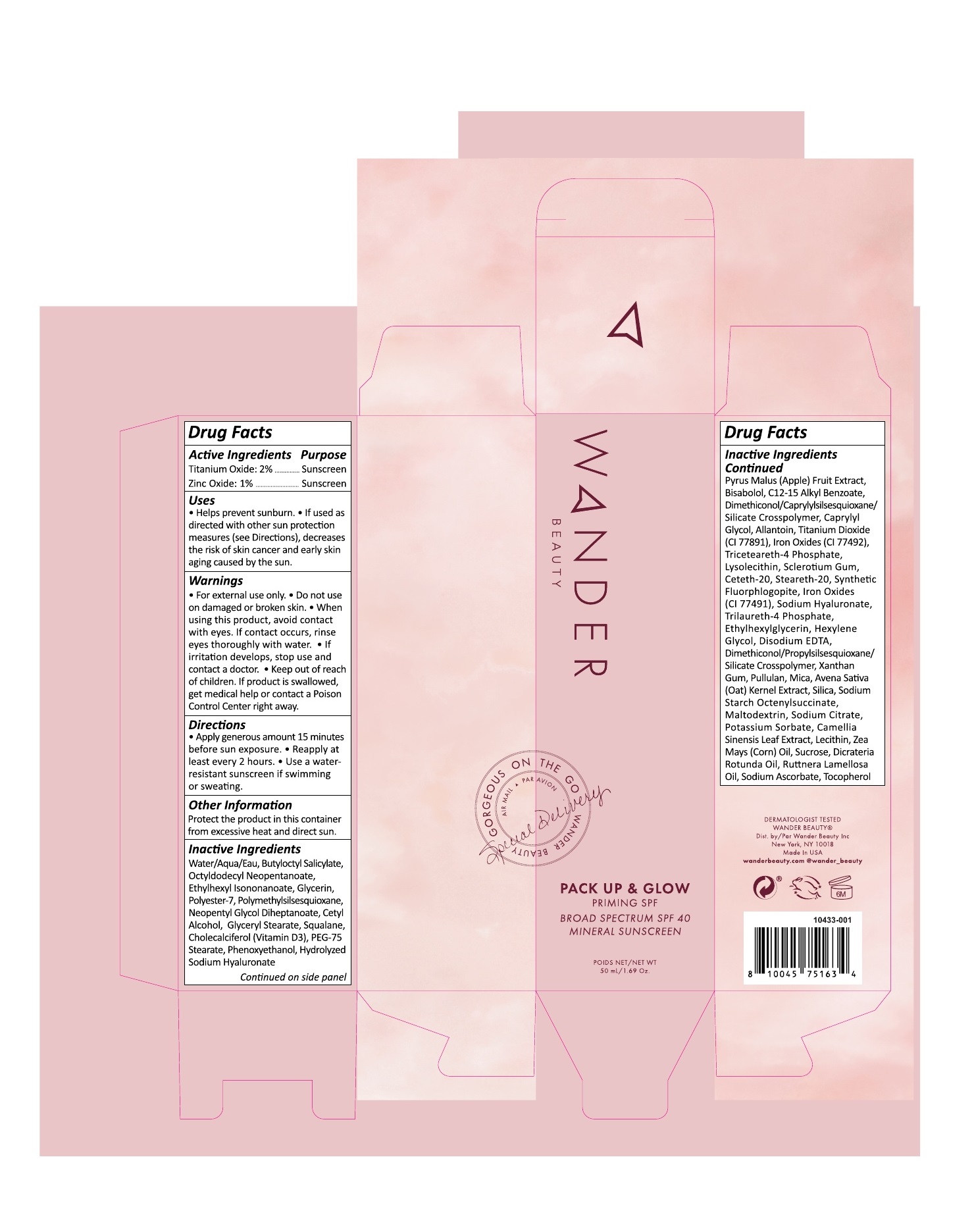 DRUG LABEL: Wander PACK UP and GLOW
NDC: 82510-000 | Form: LOTION
Manufacturer: Wander Beauty Inc.
Category: otc | Type: HUMAN OTC DRUG LABEL
Date: 20231221

ACTIVE INGREDIENTS: TITANIUM DIOXIDE 20 mg/1 mL; ZINC OXIDE 10 mg/1 mL
INACTIVE INGREDIENTS: WATER; BUTYLOCTYL SALICYLATE; OCTYLDODECYL NEOPENTANOATE; ETHYLHEXYL ISONONANOATE; GLYCERIN; POLYESTER-7; POLYMETHYLSILSESQUIOXANE (4.5 MICRONS); NEOPENTYL GLYCOL DIHEPTANOATE; CETYL ALCOHOL; GLYCERYL MONOSTEARATE; SQUALANE; CHOLECALCIFEROL; PEG-75 STEARATE; PHENOXYETHANOL; APPLE; LEVOMENOL; BENZOIC ACID; ALKYL (C12-15) BENZOATE; CAPRYLYL GLYCOL; ALLANTOIN; FERRIC OXIDE RED; TRICETEARETH-4 PHOSPHATE; BETASIZOFIRAN; CETETH-20; STEARETH-20; HYALURONATE SODIUM; TRILAURETH-4 PHOSPHATE; ETHYLHEXYLGLYCERIN; HEXYLENE GLYCOL; EDETATE DISODIUM ANHYDROUS; XANTHAN GUM; PULLULAN; MICA; OAT; SILICON DIOXIDE; MALTODEXTRIN; SODIUM CITRATE, UNSPECIFIED FORM; STANNIC OXIDE; POTASSIUM SORBATE; GREEN TEA LEAF; CORN OIL; SUCROSE; DICRATERIA ROTUNDA OIL; RUTTNERA LAMELLOSA OIL; SODIUM ASCORBATE; TOCOPHEROL

Wander PACK UP & GLOW

Active Ingredients

Titanium Dioxide 2%, Zinc Oxide 1%

Purpose

Sunscreen

Uses

• Helps prevent sunburn. • If used as directed with other sun protection measures (see Directions), decreases the risk of skin cancer and early skin aging caused by the sun.

Warnings

• For external use only.

Do not use

• on damaged or broken skin.

When using this product,

• avoid contact with eyes. If contact occurs, rinse eyes thoroughly with water. • If irritation develops, stop use and contact a doctor.

Keep out of reach of children.

• If product is swallowed, get medical help or contact a Poison Control Center right away.

Directions

Apply generous amount 15 minutes before sun exposure.

Inactive Ingredients

Water/Aqua/Eau, Butyloctyl Salicylate, Octyldodecyl Neopentanoate, Ethylhexyl Isononanoate, Glycerin, Polyester-7, Polymethylsilsesquioxane, Neopentyl Glycol Diheptanoate, Cetyl Alcohol, Glyceryl Stearate, Squalane, Cholecalciferol (Vitamin D3), PEG-75 Stearate, Phenoxyethanol, Hydrolyzed Sodium Hyaluronate, Pyrus Malus (Apple) Fruit Extract, Bisabolol, C12-15 Alkyl Benzoate, Dimethiconol/ Caprylylsilsesquioxane /Silicate Crosspolymer, Caprylyl Glycol, Allantoin, Titanium Dioxide (CI 77891), Iron Oxides (CI 77492), Triceteareth-4 Phosphate, Lysolecithin, Sclerotium Gum, Ceteth-20, Steareth-20, Synthetic Fluorphlogopite, Iron Oxides (CI 77491), Sodium Hyaluronate, Trilaureth-4 Phosphate,
Ethylhexylglycerin, Hexylene Glycol, Disodium EDTA, Dimethiconol/Propylsilsesquioxane/Silicate Crosspolymer, Xanthan Gum, Pullulan, Mica, Avena Sativa (Oat) Kernel Extract, Silica, Sodium Starch Octenylsuccinate, Maltodextrin, Sodium Citrate, Tin Oxide, Potassium Sorbate, Camellia Sinensis Leaf Extract, Lecithin, Zea Mays (Corn) Oil, Sucrose, Dicrateria Rotunda Oil, Ruttnera Lamellosa Oil, Sodium Ascorbate, Tocopherol

Other Information

Protect the product in this container from excessive heat and direct sun.